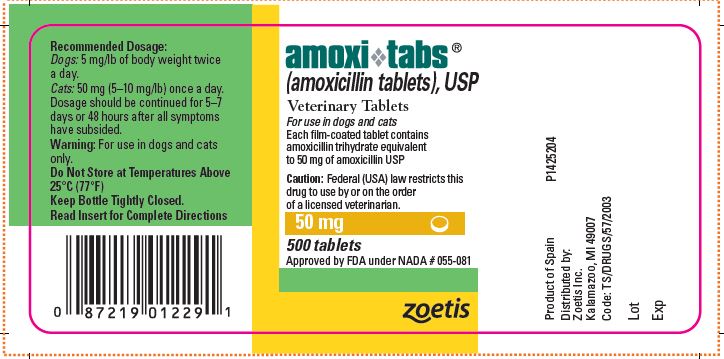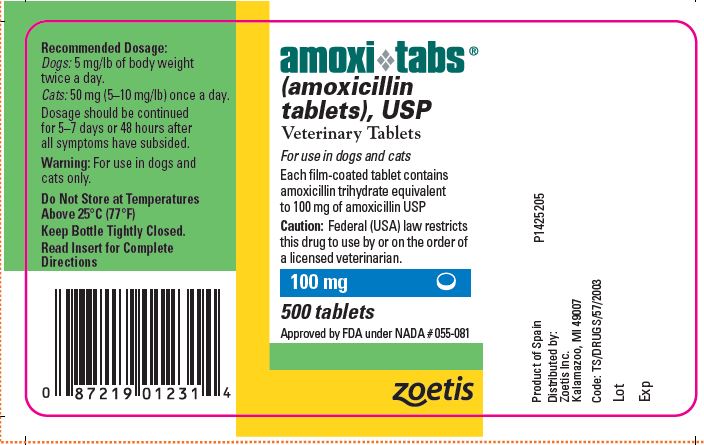 DRUG LABEL: Amoxi-Tabs
NDC: 54771-6042 | Form: TABLET, FILM COATED
Manufacturer: Zoetis Inc.
Category: animal | Type: PRESCRIPTION ANIMAL DRUG LABEL
Date: 20241114

ACTIVE INGREDIENTS: AMOXICILLIN 50 mg/1 1

amoxi❖tabs®
(amoxicillin tablets), USP
Veterinary Tablets

For use in dogs and cats

CAUTION

Federal law restricts this drug to use by or on the order of a licensed veterinarian

DESCRIPTION

Amoxi-Tabs (amoxicillin tablets) is a semisynthetic antibiotic with a broad spectrum of activity. It provides bactericidal activity against a wide range of common gram-positive and gram-negative pathogens. Chemically, it is D(-)-a-amino-p-hydroxybenzyl penicillin trihydrate.

CLINICAL PHARMACOLOGY

Amoxi-Tabs is stable in the presence of gastric acid and may be given without regard to meals. It is rapidly absorbed after oral administration. It diffuses readily into most body tissues and fluids with the exception of brain and spinal fluid, except when meninges are inflamed. Most of the amoxicillin is excreted unchanged in the urine.

Amoxicillin is similar to ampicillin in its bactericidal action against susceptible organisms. It acts through the inhibition of biosynthesis of cell wall mucopeptide. In vitro and/or in vivo studies have demonstrated the susceptibility of most strains of the following gram-positive and gram-negative bacteria: a- and b-haemolytic streptococci, nonpenicillinase-producing staphylococci, Streptococcus faecalis, Escherichia coli, and Proteus mirabilis. Because it does not resist destruction by penicillinase, it is not effective against penicillinase-producing bacteria, particularly resistant staphylococci. All strains of Pseudomonas and most strains of Klebsiella and Enterobacter are resistant

INDICATIONS AND USAGE

Dogs:Amoxi-Tabs are indicated in the treatment of susceptible strains of the organisms causing the following infections:

Respiratory tract infections (tonsillitis, tracheobronchitis) due to Staphylococcus aureus, Streptococcus spp., E. coli, and Proteus mirabilis.

Genitourinary tract infections (cystitis) due to Staphylococcus aureus, Streptococcus spp., E. coli, and Proteus mirabilis.

Gastrointestinal tract infections (bacterial gastroenteritis) due to Staphylococcus aureus, Streptococcus spp., E. coli, and Proteus mirabilis.

Bacterial dermatitis due to Staphylococcus aureus, Streptococcus spp., and Proteus mirabilis.

Soft tissue infections (abscesses, lacerations,and wounds) due to Staphylococcus aureus, Streptococcus spp., E. coli, and Proteus mirabilis.

Cats:Amoxi-Tabs are indicated in the treatment of susceptible strains of the organisms causing the following infections:

Upper respiratory tract infections due to Staphylococcus aureus, Streptococcus spp., and E. coli.

Genitourinary tract infections (cystitis) due to Staphylococcus aureus, Streptococcus spp., E. coli, and Proteus mirabilis.

Gastrointestinal tract infections due to E. coli.

Skin and soft tissue infections (abscesses, lacerations, and wounds) due to Staphylococcus aureus, Streptococcus spp., E. coli, and Pasteurella multocida.

As with all antibiotics, appropriate in vitro culturing and susceptibility testing of samples taken before treatment should be conducted.

CONTRAINDICATIONS

The use of this drug is contraindicated in animals with a history of an allergic reaction to penicillin.

WARNING

For use in dogs and cats only

ADVERSE REACTIONS

Amoxicillin is a semisynthetic penicillin and has the potential for producing allergic reactions. If an allergic reaction occurs, administer epinephrine and/or steroids

DOSAGE AND ADMINISTRATION

Dogs: The recommended dosage is 5 mg/lb of body weight twice a day.

Cats: The recommended dosage is 50 mg (5–10 mg/lb) once a day.

Dosage should be continued for 5–7 days or 48 hours after all symptoms have subsided. If no improvement is seen in 5 days, review diagnosis and change therapy.

STORAGE AND HANDLING

Do Not Store at Temperatures Above 25°C (77°F)

Keep Bottle Tightly Closed.

HOW SUPPLIED

Amoxi-Tabs are supplied in 5 strengths: 50 mg, 100 mg, 150 mg, and 200 mg in bottles of 500 tablets; 400 mg in bottles of 250 tablets.

Approved by FDA under NADA # 055-078
Approved by FDA under NADA # 055-081
zoetis
Distributed by:
Zoetis Inc.
Kalamazoo, MI 49007
P1523357
Revised: January 2020